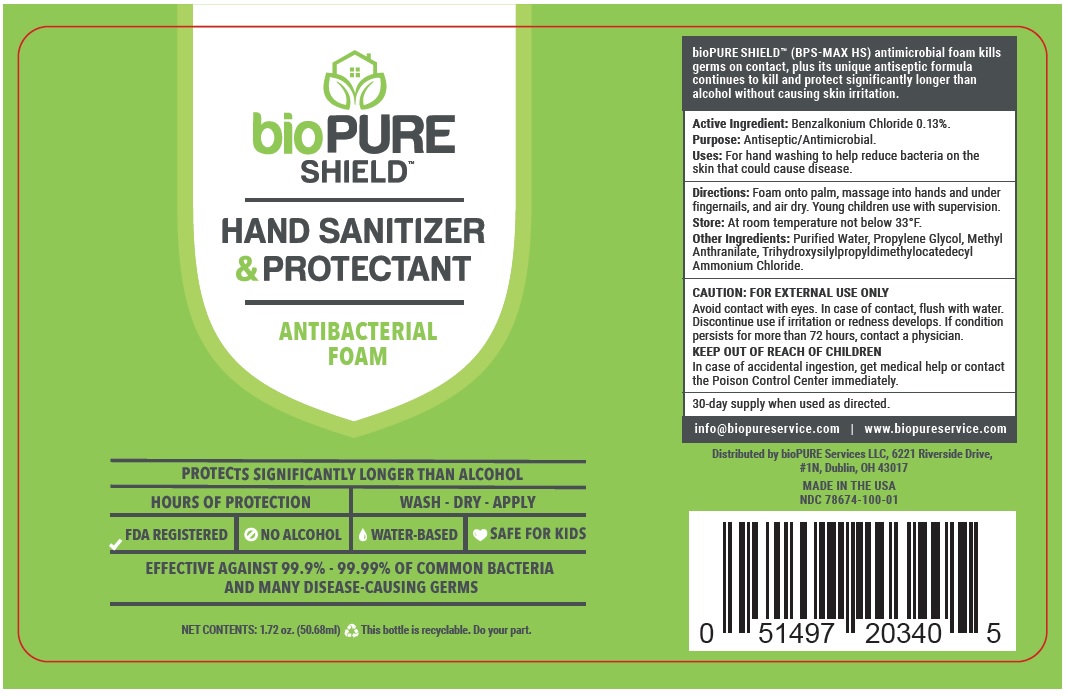 DRUG LABEL: bioPURE Shield
NDC: 78674-100 | Form: LIQUID
Manufacturer: Biopure Services Llc
Category: otc | Type: HUMAN OTC DRUG LABEL
Date: 20241014

ACTIVE INGREDIENTS: BENZALKONIUM CHLORIDE 0.13 g/100 mL
INACTIVE INGREDIENTS: WATER; PROPYLENE GLYCOL; METHYL ANTHRANILATE; OCTADECYLDIMETHYL(3-TRIHYDROXYSILYLPROPYL)AMMONIUM CHLORIDE

bioPURE SHIELD™ HAND SANITIZER & PROTECTANT

Active Ingredient: Benzalkonium Chloride 0.13%.

Purpose: Antiseptic/Antimicrobial.

INDICATIONS AND USAGE

Uses: For hand washing to help reduce bacteria on the skin that could cause disease.

DOSAGE AND ADMINISTRATION

Directions: Foam onto palm, massage into hands and under fingernails, and air dry. Young children use with supervision.

STORAGE AND HANDLING

Store: At room temperature not below 33°F.

INACTIVE INGREDIENT

Other Ingredients: Purified Water, Propylene Glycol, Methyl Anthranilate, Trihydroxysilylpropyldimethylocatedecyl Ammonium Chloride.

WARNINGS

CAUTION: FOR EXTERNAL USE ONLY
Avoid contact with eyes. In case of contact, flush with water.
Discontinue use if irritation or redness develops. If condition persists for more than 72 hours, contact a physician.

KEEP OUT OF REACH OF CHILDREN

In case of accidental ingestion, get medical help or contact the Poison Control Center immediately.

ANTIBACTERIAL FOAM

PROTECTS SIGNIFICANTLY LONGER THAN ALCOHOL

HOURS OF PROTECTION

WASH - DRY - APPLY

FDA REGISTERED

NO ALCOHOL

WATER-BASED

SAFE FOR KIDS

EFFECTIVE AGAINST 99.9% - 99.99% OF COMMON BACTERIA AND MANY DISEASE-CAUSING GERMS

This bottle is recyclable. Do your part.

bioPURE SHIELD™ (BPS-MAX HS) antimicrobial foam kills germs on contact, plus its unique antiseptic formula continues to kill and protect significantly longer than alcohol without causing skin irritation.

30-day supply when used as directed.
info@biopureservice.com | www.biopureservice.com

Distributed by bioPURE Services LLC, 6221 Riverside Drive,
#1N, Dublin, OH 43017

MADE IN THE USA